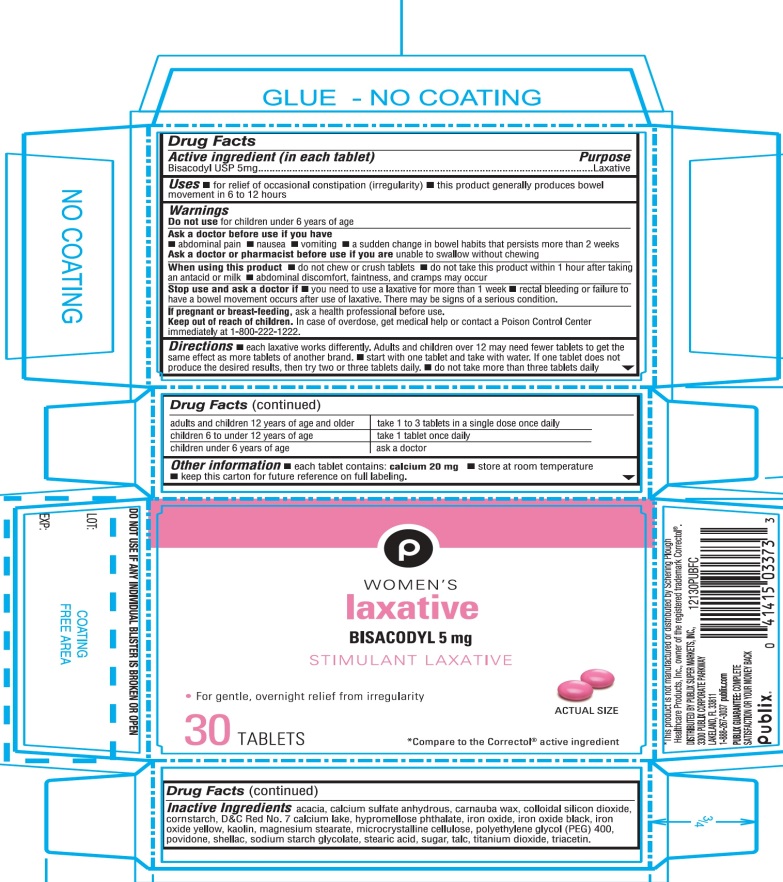 DRUG LABEL: Publix Women

NDC: 41415-121 | Form: TABLET
Manufacturer: PUBLIX SUPER MARKETS, INC
Category: otc | Type: HUMAN OTC DRUG LABEL
Date: 20251028

ACTIVE INGREDIENTS: BISACODYL 5 mg/1 1
INACTIVE INGREDIENTS: ACACIA; CALCIUM SULFATE ANHYDROUS; ANHYDROUS LACTOSE; CARNAUBA WAX; SILICON DIOXIDE; STARCH, CORN; D&C RED NO. 7; HYPROMELLOSE PHTHALATE (24% PHTHALATE, 55 CST); FERROSOFERRIC OXIDE; FERRIC OXIDE RED; FERRIC OXIDE YELLOW; KAOLIN; MAGNESIUM STEARATE; MICROCRYSTALLINE CELLULOSE; POLYETHYLENE GLYCOL 400; POVIDONE, UNSPECIFIED; SHELLAC; SODIUM STARCH GLYCOLATE TYPE A POTATO; STEARIC ACID; RAW SUGAR; TALC; TITANIUM DIOXIDE; TRIACETIN

Publix Stimulant Woman’s Laxative 30 Tablets

Active ingredient (in each tablet)

Bisacodyl, USP 5 mg

Purpose

Laxative

Use

- for relief of occasional constipation (irregularity)
- this product generally produces a bowel movement in 6 to 12 hours

Warnings

Do not use

for children under 6 years of age.

Ask a doctor before use if you have

- abdominal pain
- nausea
- vomiting
- a sudden change in bowel habits that lasts more than 2 weeks

When using this product

- do not chew or crush tablet
- do not use within 1 hour after taking an antacid or milk
- abdominal discomfort, faintness and cramps may occur

Stop use and ask a doctor if

- you need to use a laxative for more than 1 week
- rectal bleeding or failure to have a bowel movement after use of laxative. These could be signs of a serious condition.

If pregnancy or breast-feeding,

ask a health professional before use.

Keep out of reach of children.

In case of overdose, get medical help or contact a Poison Control Center right away at (1-800-222-1222).

Directions

- each laxative works differently. Adults and children over 12 may need fewer tablets to get the same effect as more tablets of another brand.
- start with one tablet and take with water. If one tablet does not produce the desired results, then try two or three tablets daily.
- do not take more than three tablets daily

adults and children 12 years of age and older | take 1 to 3 tablets in a single dose once daily
children 6 to under 12 year of age | take 1 tablets once daily
children under 6 years of age | ask a doctor

Other information

- each tablet contains: calcium 20 mg
- store at room temperature
- keep this carton for future reference on full labeling.

Inactive ingredients

acacia, calcium sulfate anhydrous, carnauba wax, colloidal silicon dioxide, corn starch, D&C Red No. 7 calcium lake, hypromellose phthalate, iron oxide, iron oxide black, iron oxide yellow, kaolin, magnesium stearate, microcrystalline cellulose, polyethylene glycol (PEG) 400, povidone, shellac, sodium starch glycolate, stearic acid, sugar, talc, titanium dioxide, triacetin.

Questions or comments?

1-888-267-3037

Principal Display Panel

NDC# 41415-121-30

*Compare to the Correctol®active ingredient

WOMEN’S laxative

BISACODYL, USP 5 mg

STIMULANT LAXATIVE

- For gentle, overnight relief from irregularity

30 TABLETS

*This product is not manufactured or distributed by Schering Plough Healthcare Products, Inc., owner of the registered trademark Correctol®.

TAMPER EVIDENT: DO NOT USE IF ANY INDIVIDUAL BLISTER IS BROKEN OR OPEN.

IMPORTANT:Keep this carton for future reference on full labeling.

DISTRIBUTED BY PUBLIX SUPER MARKETS, INC.,

3300 PUBLIX CORPORATE PARKWAY, LAKELAND, FL 33811

1-888-267-3037 publix.com

PUBLIX GUARANTEE: COMPLETE SATISFACTION OR YOUE MONEY BACK